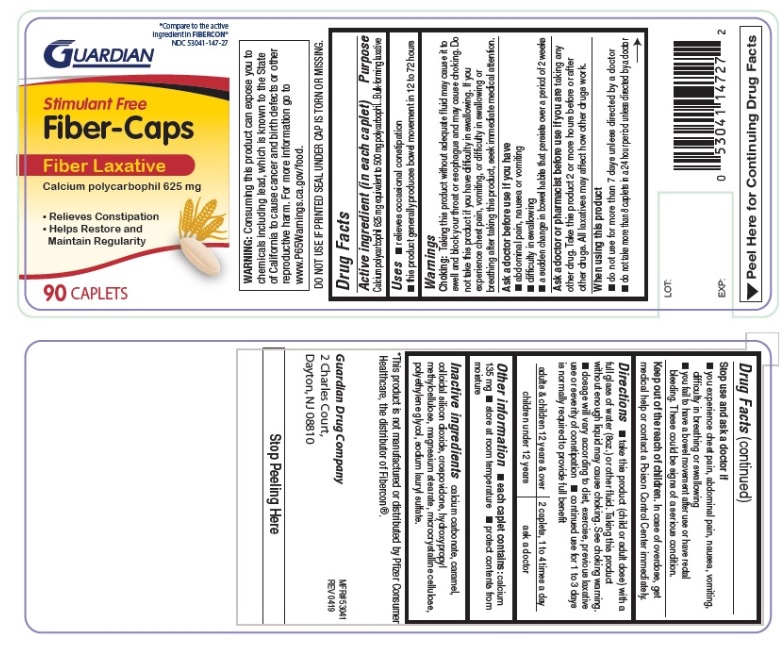 DRUG LABEL: Fiber Caps
                
NDC: 53041-147 | Form: TABLET, FILM COATED
Manufacturer: Guardian Drug Company
Category: otc | Type: HUMAN OTC DRUG LABEL
Date: 20241219

ACTIVE INGREDIENTS: CALCIUM POLYCARBOPHIL 625 mg/1 1
INACTIVE INGREDIENTS: CALCIUM CARBONATE; CARAMEL; SILICON DIOXIDE; CROSPOVIDONE; HYPROMELLOSES; MAGNESIUM STEARATE; MICROCRYSTALLINE CELLULOSE; POLYETHYLENE GLYCOL, UNSPECIFIED; SODIUM LAURYL SULFATE

Fiber-Caps

Active ingredient (in each caplet)

Calcium polycarbophil 625 mg equivalent to 500 mg polycarbophil

Purpose

Bulk-forming laxative

Uses

relieves:

- constipation
- helps restore and maintain regularity
- promotes normal function of the bowel
- this product generally produces bowel movement in 12 to 72 hours

Keep out of reach of children. In case of overdose, get medical help or contact a Poison Control Center immediately.

Warnings

Choking: Taking this product without adequate fluid may cause it to swell and block your throat or esophagus and may cause choking. Do not take this product if you have difficulty in swallowing. If you experience chest pain, vomiting, or difficulty in swallowing or breathing after taking this product, seek immediate medical attention.

Ask a doctor before use if you have

- abdominal pain, nausea or vomiting
- difficulty in swallowing
- a sudden change in bowel habits that persists over a period of 2 weeks

Ask a doctor or pharmacist before use if you are

taking any other drug. Take this product 2 or more hours before or after other drugs. All laxatives may affect how other drugs work

When using this product

- do not use for more than 7 days unless directed by a doctor
- do not take more than 8 caplets in a 24 hour period unless directed by a doctor

Stop use and ask a doctor if

- you experience chest pain, abdominal pain, nausea, vomiting, difficulty in breathing or swallowing
- you fail to have a bowel movement after use
- rectal bleeding occurs

Directions

- take this product (child or adult dose) with a full glass of water (8oz.) or other fluid. Taking this product without enough liquid may cause choking. See choking warning.

- dosage will vary according to diet, exercise, previous laxative use or severity of constipation
- continued use for 1 to 3 days is normally required to provide full benefit

adults and children over 12 years | 2 caplets, 1 to 4 times a day
children under 12 years | ask a doctor

Other information

- each caplet contains: calcium 135 mg
- do not use if printed seal under cap is torn or missing
- store at room temperature
- protect contents from moisture

Inactive ingredients

calcium carbonate, caramel, colloidal silicon dioxide, crospovidone, hydroxypropyl methylcellulose, magnesium stearate, microcrystalline cellulose, polyethylene glycol, sodium lauryl sulfate

Principal Display Panel

Compare to the active ingredient in FIBERCON

NDC 53041-147-27

Stimulant Free

Fiber-Caps

Fiber Laxative

Calcium polycarbophil 625 mg

- Relieves constipation
- Helps Restore and Maintain Regularity